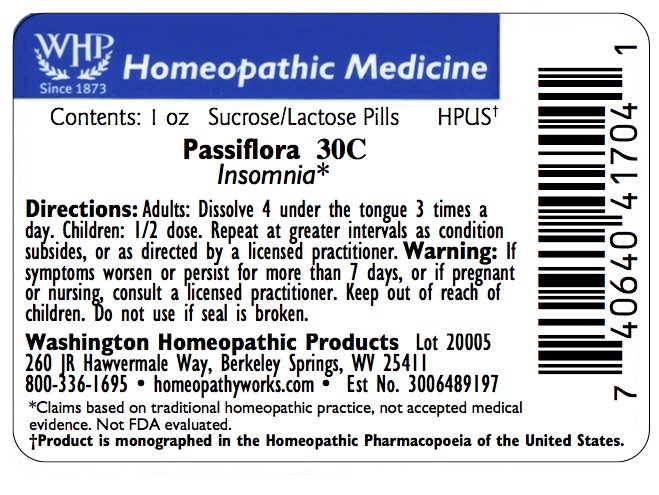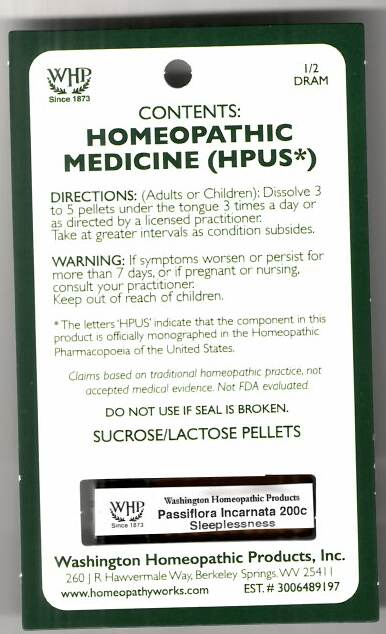 DRUG LABEL: Passiflora incarnata Kit Refill
NDC: 71919-775 | Form: PELLET
Manufacturer: Washington Homeopathic Products
Category: homeopathic | Type: HUMAN OTC DRUG LABEL
Date: 20250128

ACTIVE INGREDIENTS: PASSIFLORA INCARNATA FLOWERING TOP 200 [hp_C]/1 1
INACTIVE INGREDIENTS: SUCROSE; LACTOSE

Passiflora Incarnata Kit Refill 200C

ACTIVE INGREDIENTS

PASSIFLORA

USES

To relieve the symptoms of insomnia.

KEEP OUT OF REACH OF CHILDREN

Keep this and all medicines out of reach of children.

INDICATIONS

PASSIFLORA Insomnia

STOP USE AND ASK DOCTOR

If symptoms persist/worsen or if pregnant/nursing, stop use and consult your practitioner.

DIRECTIONS

Adults: Dissolve 3 to 5 under the tongue three times a day or as directed by Lic. Practitioner. Take at greater intervals as condition subsides. Children: Dissolve 3 to 5 under the tongue three times a day or as directed by Lic. Practitioner. Take at greater intervals as condition subsides.

INACTIVE INGREDIENTS

Sucrose/Lactose

PRINCIPAL DISPLAY PANEL

The OTC potency range of PASSIFLORA is 2x–30x, 1c–30c, 200c, 1m, 10m, 50m, and CM.
Availability is subject to change.

All WHP single remedies are made to order; thus, the labels are printed on the same label stock as the orders are filled.

‘Bottle Size’ and ‘Potency’ vary on the label depending on customer choice.

Standard bottle sizes for pellet-form remedies are 2 dram, 4 dram, 1 ounce, 2 ounce, and 4 ounce.